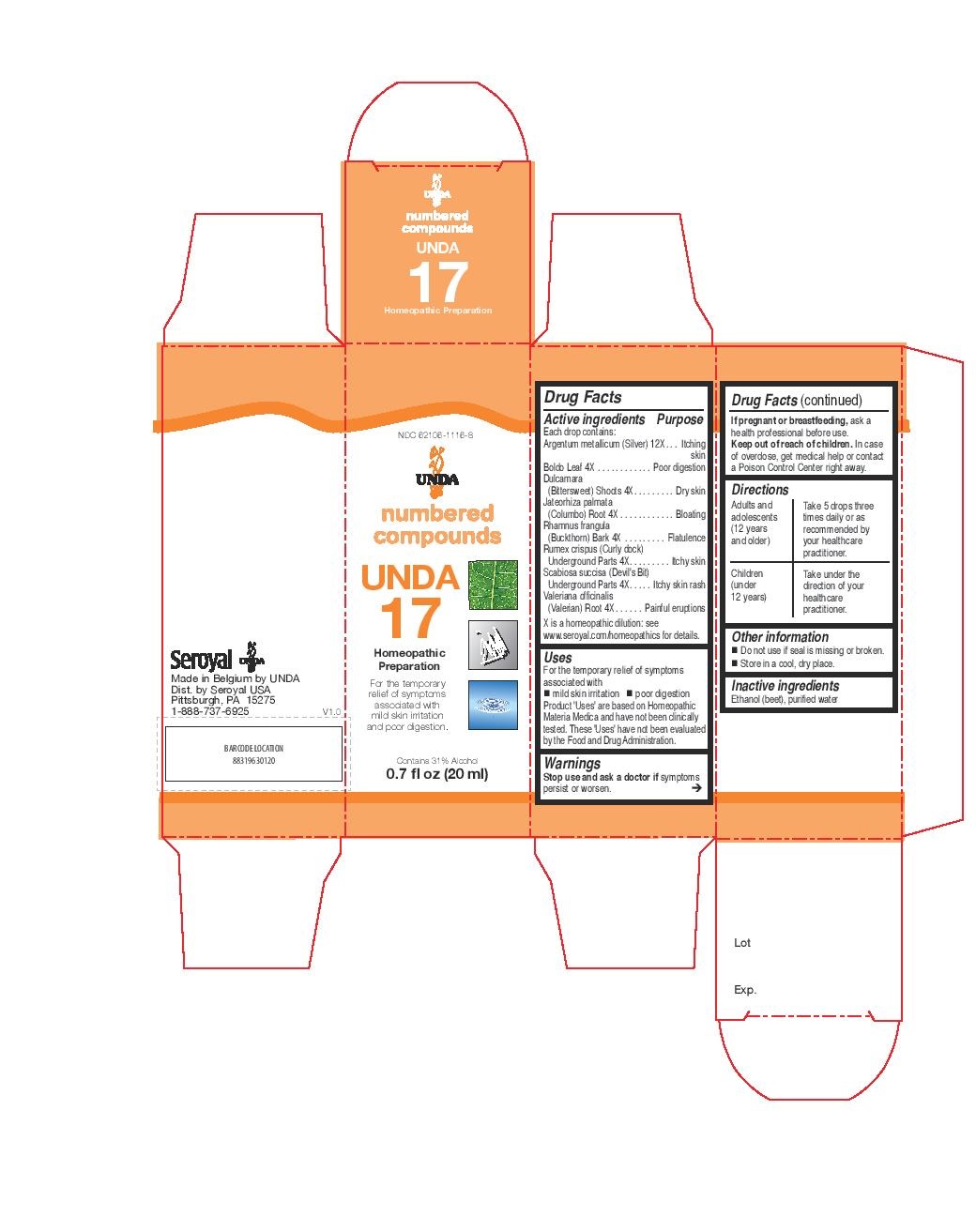 DRUG LABEL: Unda 17
NDC: 62106-1116 | Form: LIQUID
Manufacturer: Seroyal USA
Category: homeopathic | Type: HUMAN OTC DRUG LABEL
Date: 20221108

ACTIVE INGREDIENTS: JATEORHIZA CALUMBA ROOT 4 [hp_X]/20 mL; PEUMUS BOLDUS LEAF 4 [hp_X]/20 mL; FRANGULA ALNUS BARK 4 [hp_X]/20 mL; VALERIAN 4 [hp_X]/20 mL; CHAMAELIRIUM LUTEUM ROOT 4 [hp_X]/20 mL; SOLANUM DULCAMARA STEM 4 [hp_X]/20 mL; RUMEX CRISPUS ROOT 4 [hp_X]/20 mL; SILVER 12 [hp_X]/20 mL
INACTIVE INGREDIENTS: ALCOHOL; WATER

Unda 17

Active ingredients
Each drop contains:
Argentum metallicum (Silver) 12X
Boldo Leaf 4X
Dulcamara (Bittersweet) Shoots 4X
Jateorhiza palmata (Columbo) Root 4X
Rhamnus frangula (Buckthorn) Bark 4X
Rumex crispus (Curly dock) Underground Parts 4X
Scabiosa succisa (Devil's Bit) Underground Parts 4X
Valeriana officinalis (Valerian) Root 4X

Uses
For the temporary relief of symptoms associated with
mild skin irritation

poor digestion

Warnings

Stop use and ask a doctor if symptoms persist or worsen.

If pregnant or breastfeeding, ask a health professional before use.

Keep out of reach of children.

In case of overdose, get medical help or contact a
Poison Control Center right away.

PREGNANCY OR BREAST FEEDING

If pregnant or breastfeeding, ask a health professional before use.

Keep out of reach of children.

OVERDOSAGE

In case of overdose, get medical help or contact a

Poison Control Center right away.

Inactive Ingredients:

Ethanol (beet),
purified water

Directions
Adults and adolescents (12 years and older)

Take 5 drops three times daily or as recommended by your healthcare practitioner.

Children (under 12 years)

Take under the direction of your healthcare practitioner.

Uses
For the temporary relief of symptom sassociated with
mild skin irritation

poor digestion

Directions
Adults and adolescents (12 years and older)

Take 5 drops three times daily or as recommended by your healthcare practitioner.

Children (under 12 years)

Take under the direction of your healthcare practitioner.

Other information
Do not use if seal is missing or broken.
Store in a cool, dry place.

PACKAGE LABEL

NDC 62106-1116-8

UNDA

numbered compounds

UNDA 17

Homeopathic Preparation

For the temporary relief of symptoms

associated with mild skin irritation

and poor digestion.

Contains 31% Alcohol
0.7 fl oz (20 ml)